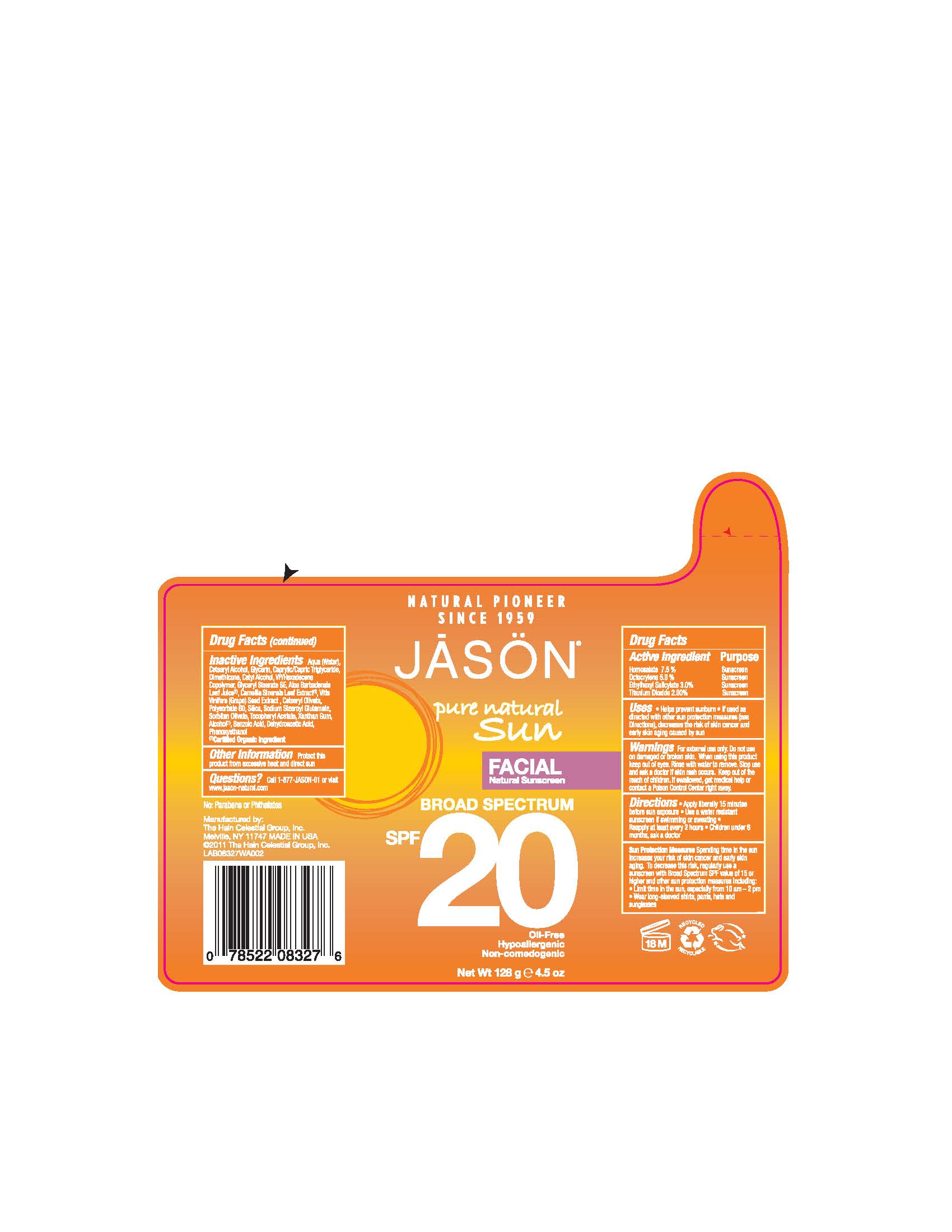 DRUG LABEL: Jason Facial Natural Sunscreen Broad Spectrum SPF20
NDC: 61995-0209 | Form: LOTION
Manufacturer: The Hain Celestial Group, Inc.
Category: otc | Type: HUMAN OTC DRUG LABEL
Date: 20120626

ACTIVE INGREDIENTS: HOMOSALATE 7.5 g/100 g; OCTOCRYLENE 5.0 g/100 g; OCTISALATE   3.0 g/100 g; TITANIUM DIOXIDE     2.0 g/100 g
INACTIVE INGREDIENTS: WATER; MEDIUM-CHAIN TRIGLYCERIDES; GLYCERIN; CETOSTEARYL ALCOHOL; ALOE VERA LEAF; DIMETHICONE; CETYL ALCOHOL    ; GLYCERYL STEARATE SE    ; VITIS VINIFERA SEED    ;  GREEN TEA LEAF      ; CETEARYL OLIVATE    ; POLYSORBATE 60; SODIUM STEAROYL GLUTAMATE; SORBITAN OLIVATE    ; SILICON DIOXIDE ; XANTHAN GUM    ; .ALPHA.-TOCOPHEROL ACETATE        ; ALCOHOL; BENZOIC ACID; DEHYDROACETIC ACID; PHENOXYETHANOL

Drug Facts

ACTIVE INGREDIENT

Homosalate 7.5%
Octocrylene 5.0%
Ethylhexyl Salicylate 3.0%

Titanium Dioxide 2.0%

PURPOSE

Sunscreens

INDICATIONS AND USAGE

- Helps prevent sunburns
- If used as directed with other sun protection measures, decreases the risk of skin cancer and early skin aging, caused by the sun.

WARNINGS

For external use only. Do not use on damaged or broken skin. When using this product keep out of eyes.Rinse with water to remove. Stop use and ask a doctor if skin rash occurs.

Keep out of reach of children. If swallowed, get medical help or contact a Poison Control Center right away.

DOSAGE AND ADMINISTRATION

- Apply liberally 15 minutes before sun exposure. Use a water resisting sunscreen if of swimming or sweating. Reapply at least every 2 hours. Children under 6 months, ask a doctor . Skin Protection Measures: Spending time in the sun increases your risk of skin cancer and early skin aging.To decrease risk, regularly use a sunscreen with Broad Spectrum SPF 15 or higher and other protective measures including:

- Limit time in the sun, especially from 10am to 2pm
- Wear long-sleeved shirts, pants, hats and sunglasses.

INACTIVE INGREDIENT

Aqua (Water), Cetearyl Alcohol, Glycerin, Caprylic/Capric Triglycerides, Dimethicone, Cetyl Alcohol, VP/Hexadecene Copolymer, Glyceryl Stearate SE, Aloe Barbadensis Leaf Juice (1),Camellia Sinensis Leaf Extract (1),Vitis Vinifera (Grape) Seed) Extract, Cetearyl Olivate, Polysorbate 60, Silica, Sodium Stearoyl Glutamate, Sorbitan Olivate,Tocopheryl Acetate, Xanthan Gum, Alcohol (1), Benzoic Acid, Dehydroacetic Acid, Phenoxyethanol,

(1) Certified Organic Ingredients

QUESTIONS

Questions? Call 1-877-JASON-01or visit www.jason-natural.com